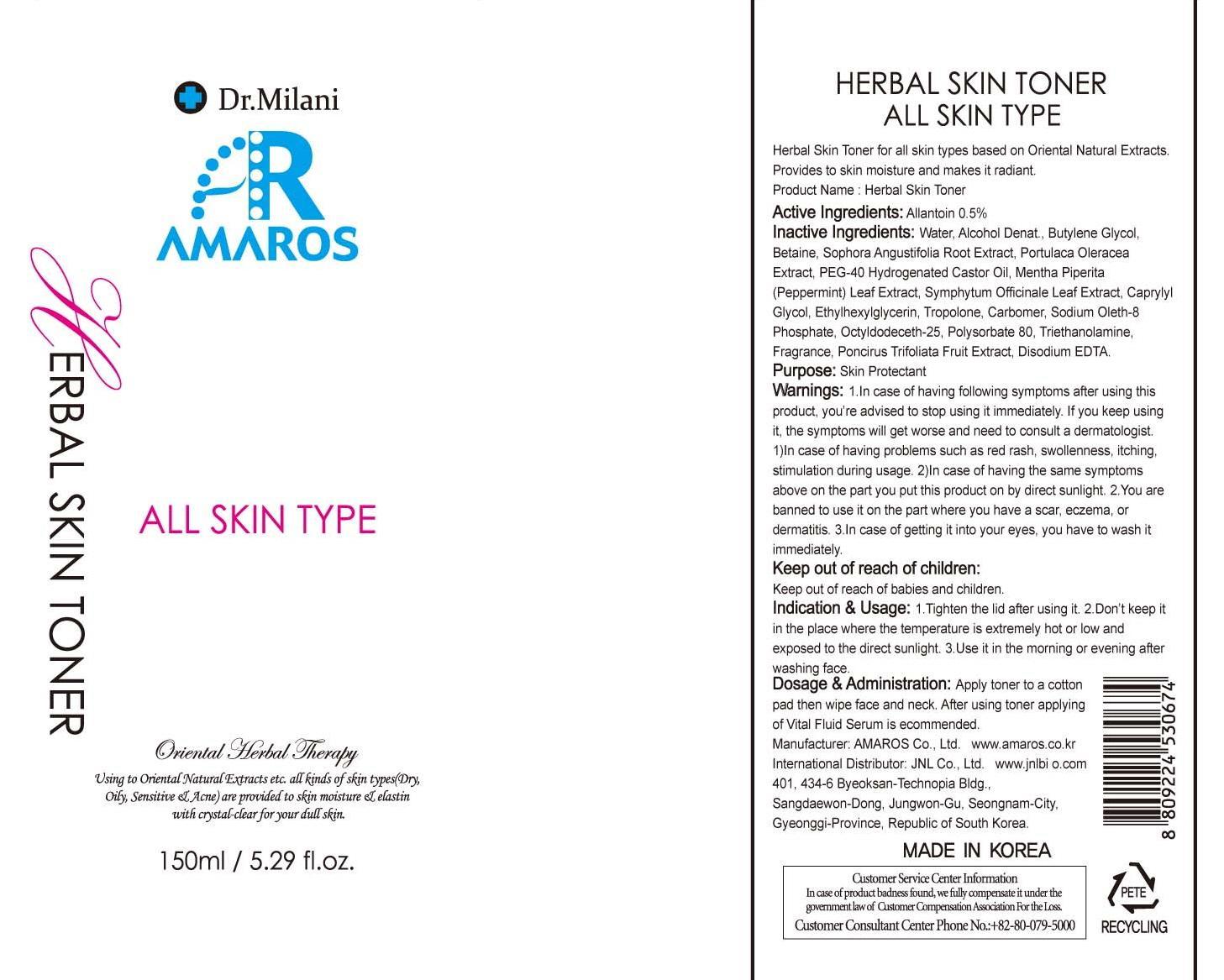 DRUG LABEL: Herbal Skin Toner
NDC: 60899-060 | Form: CREAM
Manufacturer: AMAROS CO., LTD.
Category: otc | Type: HUMAN OTC DRUG LABEL
Date: 20190411

ACTIVE INGREDIENTS: Allantoin 0.75 mg/150 mL
INACTIVE INGREDIENTS: Water; Betaine

ACTIVE INGREDIENT

Active Ingredient: Allantoin 0.5%

INACTIVE INGREDIENT

Inactive Ingredients: Water, Alcohol Denat., Butylene Glycol, Betaine, Sophora Angustifolia Root Extract, Portulaca Oleracea Extract, PEG-40 Hydrogenated Castor Oil, Mentha Piperita (Peppermint) Leaf Extract, Symphytum Officinale Leaf Extract, Caprylyl Glycol, Ethylhexylglycerin, Tropolone, Carbomer, Sodium Oleth-8 Phosphate, Octyldodeceth-25, Polysorbate 80, Triethanolamine, Fragrance, Poncirus Trifoliata Fruit Extract, Disodium EDTA.

PURPOSE

Purpose: Skin Protectant

WARNINGS

Warnings: 1. In case of having following symptoms after using this product, you're advised to stop using it immediately. If you keep using it, the symptoms will get worse and need to consult a dermatologist . 1) In case of having problems such as red rash, swollenness, itching, stimulation during usage. 2) In case of having the same symptoms above on the part you put this product on by direct sunlight. 2. You are banned to use it on the part where you have a scar, eczema, or dermatitis. 3. In case of getting it into your eyes, you have to wash it immediately.

Keep out of reach of children: Keep out of reach of babies and children.

INDICATIONS AND USAGE

Indication and Usage: 1. Tighten the lid after using it. 2. Don't keep it in the place where the temperature is extremely hot or low and exposed to the direct sunlight. 3. Use it in the morning or evening after washing face.

Dosage and Administration: Apply toner to a cotton pad then wipe face and neck. After using toner applying of Vital Fluid Serum is recommended.